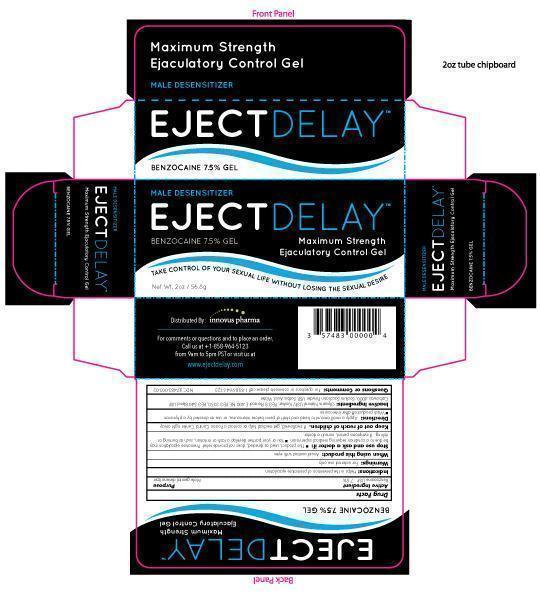 DRUG LABEL: EJECTDELAY
NDC: 57483-003 | Form: GEL
Manufacturer: Innovus Pharmaceuticals, Inc.
Category: otc | Type: HUMAN OTC DRUG LABEL
Date: 20131106

ACTIVE INGREDIENTS: Benzocaine 7.5 g/100 g
INACTIVE INGREDIENTS: Glycerin; POLYETHYLENE GLYCOL 400; POLYETHYLENE GLYCOL 3350  ; POLYETHYLENE GLYCOL 4000 ; SACCHARIN SODIUM  ; SORBIC ACID  ; Water

Drug Facts

Active Ingredients

Benzocaine 7.5%

Purpose

Male genital desensitizer

Indications

Helps in the prevention of premature ejaculation

Warnings

For external use only

When using this product

Avoid contact with eyes

Stop use and ask a doctor if

- Premature ejaculation may be due to a condition requiring medical supervision
- This product, used as directed, does not provide relief, discontinue use and consult a physician
- You or your partner develop a rash or irritation, such as burning or itching, discontinue use
- If symptoms persist, consult a doctor

Keep out of reach of children

If swallowed, get medical help or contact a Poison Control Center right away

Directions

Apply a small amount to head and shaft of penis before intercourse, or use as directed by a physician.

Wash product off after intercourse

Inactive Ingredients

Glycerin Natural USP Kosher, PEG 8 Pluracol E 400 NF, PEG 3350, PEG 540 Blend USP, Carbowax 4000, Sodium Saccharin Powder USP, Sorbic Acid, Water

Questions or Comments

For questions or comments please call 1-858-964-5123